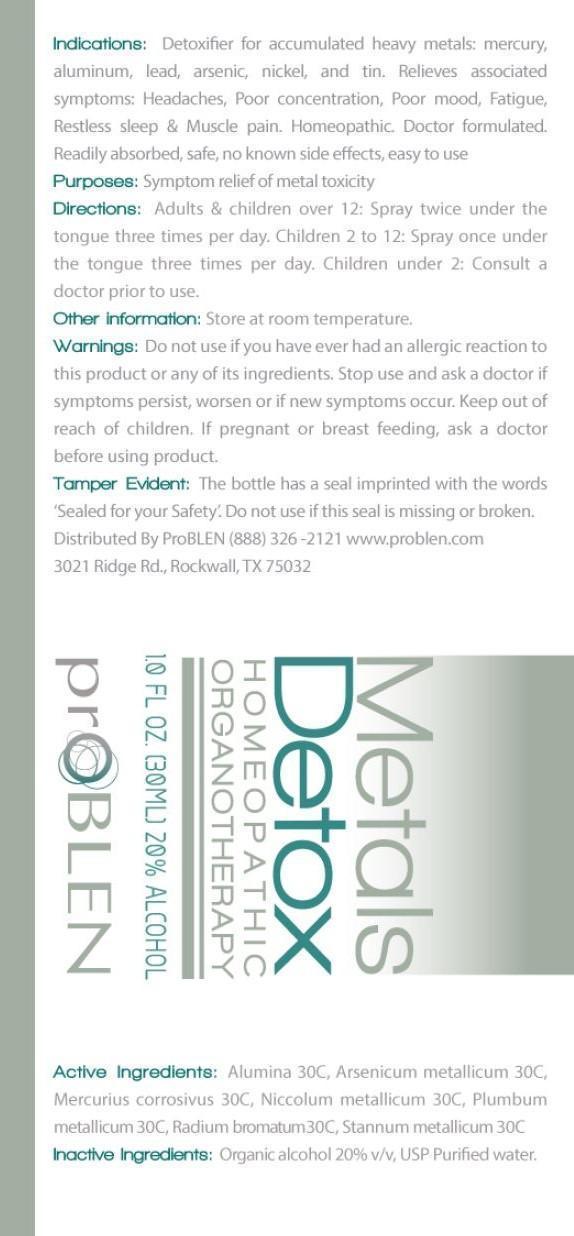 DRUG LABEL: Metals Detox
NDC: 43853-0016 | Form: SPRAY
Manufacturer: Problen Pharmacy
Category: homeopathic | Type: HUMAN OTC DRUG LABEL
Date: 20150622

ACTIVE INGREDIENTS: ALUMINUM OXIDE 30 [hp_C]/28 g; ARSENIC 30 [hp_C]/28 g; MERCURIC CHLORIDE 30 [hp_C]/28 g; NICKEL 30 [hp_C]/28 g; LEAD 30 [hp_C]/28 g; RADIUM BROMIDE 30 [hp_C]/28 g; TIN 30 [hp_C]/28 g
INACTIVE INGREDIENTS: ALCOHOL; WATER

ACTIVE INGREDIENT

Active Ingredients: alumina 30C, arsenicum metallicum 30C, mercurius corrosivus 30C, niccolum metallicum 30C, plumbum metallicum 30C, radium bromatum 30C, stannum metallicum 30C

PURPOSE

Purposes: symptom relief of metal toxicity

Keep out of reach of children.

INDICATIONS AND USAGE

Indications: Detoxifier for accumulated heavy metals: mercury, aluminum, lead, arsenic, nickel, and tin. Relieves associated symptoms: headaches, poor concentration, poor mood, fatigue, restless sleep & muscle pain. Homeopathic. Doctor formulated. Readily absorbed, safe, no known side effects, easy to use.

DOSAGE AND ADMINISTRATION

Directions: Adults & children over 12: spray twice under the tongue three times per day. Children 2 to 12: spray once under the tongue three times per day. Children under 2: consult a doctor prior to use.

WARNINGS

Warnings: Do not use if you have ever had an allergic reaction to this product or any of its ingredients. Stop use and ask a doctor if symptoms persist, worsen or if new symptoms occur. If pregnant or breast feeding, ask a doctor before using product.

Other information: Store at room temperature.

Tamper Evident: The bottle has a seal imprinted with the words "sealed for your safety." Do not use if this seal is missing or broken.

INACTIVE INGREDIENT

Inactive Ingredients: organic alcohol 20% v/v, USP purified water.